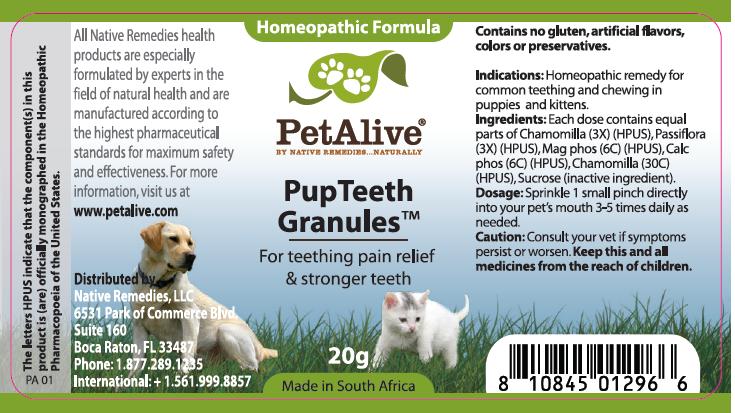 DRUG LABEL: PupTeeth 
NDC: 50048-105 | Form: GRANULE
Manufacturer: W. Last CC
Category: homeopathic | Type: OTC ANIMAL DRUG LABEL
Date: 20111115

ACTIVE INGREDIENTS: MATRICARIA RECUTITA 3 [hp_X]/20 g; PASSIFLORA INCARNATA FLOWERING TOP 3 [hp_X]/20 g; MAGNESIUM PHOSPHATE 6 [hp_C]/20 g; CALCIUM PHOSPHATE 6 [hp_C]/20 g; MATRICARIA RECUTITA 30 [hp_C]/20 g
INACTIVE INGREDIENTS: SUCROSE

ACTIVE INGREDIENT

Each dose contains equal parts of Chamomilla (3X) (HPUS), Passiflora (3X) (HPUS), Mag phos (6C) (HPUS), Calc phos (6C) (HPUS), Chamomilla (30C) (HPUS)

PURPOSE

For teething pain relief and stronger teeth

INDICATIONS AND USAGE

Homeopathic remedy for common teething and chewing in puppies and kittens.

DOSAGE AND ADMINISTRATION

Sprinkle 1 small pinch directly into your pet’s mouth 3-5 times daily as needed.

WARNINGS

Consult your vet if symptoms persist or worsen.

KEEP OUT OF REACH OF CHILDREN

Keep this and all medicines from the reach of children.